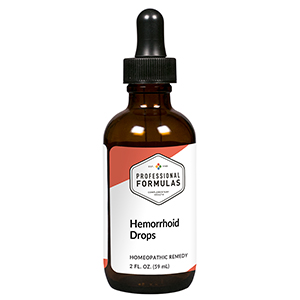 DRUG LABEL: Hemorrhoid Drops
NDC: 63083-2028 | Form: LIQUID
Manufacturer: Professional Complementary Health Formulas
Category: homeopathic | Type: HUMAN OTC DRUG LABEL
Date: 20190815

ACTIVE INGREDIENTS: HORSE CHESTNUT 2 [hp_X]/59 mL; HAMAMELIS VIRGINIANA ROOT BARK/STEM BARK 3 [hp_X]/59 mL; ACHILLEA MILLEFOLIUM WHOLE 3 [hp_X]/59 mL; PAEONIA OFFICINALIS ROOT 3 [hp_X]/59 mL; COLLINSONIA CANADENSIS ROOT 4 [hp_X]/59 mL; STRYCHNOS NUX-VOMICA SEED 4 [hp_X]/59 mL; LYCOPODIUM CLAVATUM SPORE 5 [hp_X]/59 mL; SULFUR 5 [hp_X]/59 mL; ALOE 6 [hp_X]/59 mL; POTASSIUM CARBONATE 6 [hp_X]/59 mL; NITRIC ACID 6 [hp_X]/59 mL; GRAPHITE 8 [hp_X]/59 mL
INACTIVE INGREDIENTS: ALCOHOL; WATER

C28

ACTIVE INGREDIENTS

Aesculus hippocastanum 2X
Hamamelis virginiana 3X
Millefolium 3X
Paeonia officinalis 3X
Collinsonia canadensis 4X
Nux vomica 4X
Lycopodium clavatum 5X
Sulphur 5X
Aloe socotrina 6X
Kali carbonicum 6X
Nitricum acidum 6X
Graphites 8X

QUESTIONS

Professional Formulas

PO Box 2034 Lake Oswego, OR 97035

INDICATIONS

For the temporary relief of itching, swelling, or discomfort associated with hemorrhoids.*

PURPOSE

*Claims based on traditional homeopathic practice, not accepted medical evidence. Not FDA evaluated.

WARNINGS

Do not use for more than 30 days. Keep out of the reach of children. In case of overdose, get medical help or contact a poison control center right away. If pregnant or breastfeeding, ask a healthcare professional before use.

Keep out of the reach of children.

PREGNANCY OR BREAST FEEDING

If pregnant or breastfeeding, ask a healthcare professional before use.

DIRECTIONS

Place drops under tongue 30 minutes before/after meals. Adults and children 12 years and over: Take 10 drops up to 3 times per day for up to 6 weeks. For immediate onset of symptoms, take 10 to 15 drops every 15 minutes up to 3 hours. For less severe symptoms, take 10-15 drops hourly up to 8 hours. Consult a physician for use in children under 12 years of age.

OTHER INFORMATION

Tamper resistant. If seal is broken, do not use. After opening, close container tightly and store at room temperature away from heat.

INACTIVE INGREDIENTS

20% ethanol, purified water.

LABEL

Est 1985

Professional Formulas

Complementary Health

Hemorrhoid Drops

Homeopathic Remedy

2 FL. OZ. (59 mL)